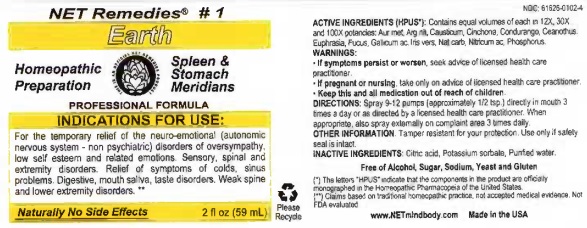 DRUG LABEL: Earth
NDC: 61626-0102 | Form: LIQUID
Manufacturer: NET Remedies
Category: homeopathic | Type: HUMAN OTC DRUG LABEL
Date: 20210119

ACTIVE INGREDIENTS: GOLD 12 [hp_X]/59 mL; SILVER NITRATE 12 [hp_X]/59 mL; CAUSTICUM 12 [hp_X]/59 mL; CINCHONA OFFICINALIS BARK 12 [hp_X]/59 mL; MARSDENIA CONDURANGO BARK 12 [hp_X]/59 mL; CEANOTHUS AMERICANUS LEAF 12 [hp_X]/59 mL; EUPHRASIA STRICTA 12 [hp_X]/59 mL; FUCUS VESICULOSUS 12 [hp_X]/59 mL; GALLIC ACID MONOHYDRATE 12 [hp_X]/59 mL; IRIS VERSICOLOR ROOT 12 [hp_X]/59 mL; SODIUM CARBONATE 12 [hp_X]/59 mL; NITRIC ACID 12 [hp_X]/59 mL; PHOSPHORUS 12 [hp_X]/59 mL
INACTIVE INGREDIENTS: CITRIC ACID MONOHYDRATE; POTASSIUM SORBATE; WATER

Earth

ACTIVE INGREDIENT

ACTIVE INGREDIENTS (HPUS*): Contains equal volume of each in 12X, 30X, and 100X potencies: Aur mur, Arg nit, Causticum, Cinchona, Condurango, Ceanothus, Euphrasia, Fucus, Gallicum ac, Iris vers, Nat carb, Nitricum ac, Phosphorus.

(*) The letters "HPUS" indicate that the components in the product are officially monographed in the Homeopathic Pharmacopeia of the United States.

(**) Claims based on traditional homeopathic practice, not accepted medical evidence. Not FDA evaluated.

INDICATIONS FOR USE:

For the temporary relief of the neuro-emotional (automatic nervous system - non psychiatric) disorders of oversympathy, low self esteem and related emotions. Sensory, spinal and extremity disorders. Relief of symptoms of colds, sinus problems. Digestive, mouth saliva, taste disorders. Weak spine and lower extremity disorders.**

WARNINGS:

• If symptoms persist or worsen, seek advice of licensed health care practicioner.

• If pregnant or nursing, take only on advice of licensed health care practicioner.

• Keep this and all medication out of reach of children.

KEEP OUT OF REACH OF CHILDREN

• Keep this and all medication out of reach of children.

DOSAGE AND ADMINISTRATION

DIRECTIONS: Spray 9-12 pumps (approximately 1/2 tsp.) directly in mouth 3 times a day or as directed by a licensed health care practicioner. When appropriate, also spray externalyl on complaint area 3 times daily.

OTHER INFORMATION: Tamper resistant for your protection. Use only if safe seal is intact.

INACTIVE INGREDIENTS: Citric acid, Potassium sorbate, Purified water.

QUESTIONS

www.NETmindbody.com

Made in the USA

PACKAGE LABEL

NET Remedies #1

Earth

Homeopathic Preparation

Spleen & Stomach Meridans

PROFESSIONAL FORMULA

Naturally No Side Effects

2 fl oz (59 mL)

PURPOSE

For the temporary relief of the neuro-emotional (automatic nervous system - non psychiatric) disorders of oversympathy, low self esteem and related emotions. Sensory, spinal and extremity disorders. Relief of symptoms of colds, sinus problems. Digestive, mouth saliva, taste disorders. Weak spine and lower extremity disorders.**